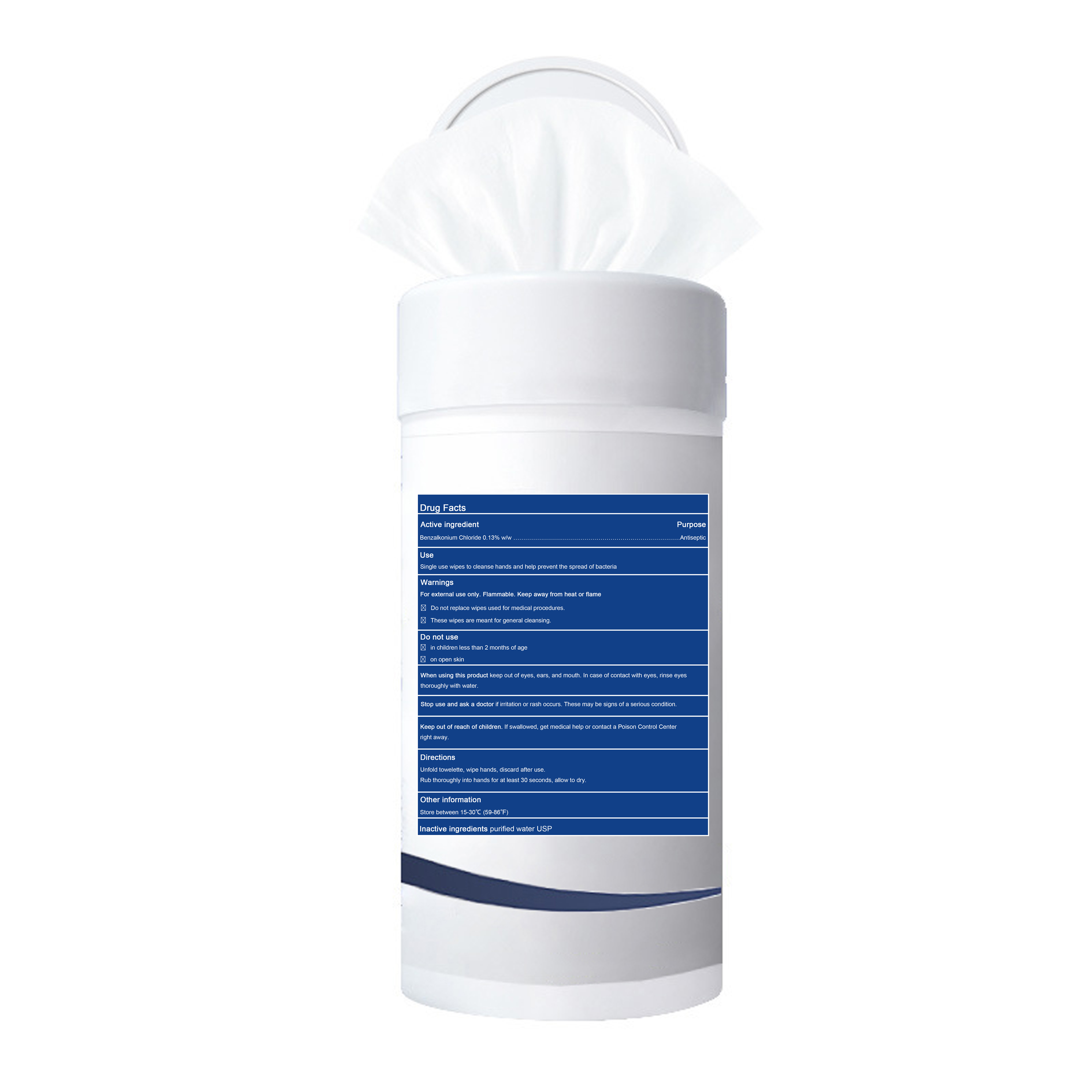 DRUG LABEL: Antiseptic sanitizing wipes (0.13% Benzalkonium Chloride)
NDC: 79846-151 | Form: CLOTH
Manufacturer: Jintu Handicraft Factory
Category: otc | Type: HUMAN OTC DRUG LABEL
Date: 20201112

ACTIVE INGREDIENTS: BENZALKONIUM CHLORIDE 5.2 mg/1 1
INACTIVE INGREDIENTS: WATER

JinTu, Wipes, Benzalkonium chloride

Active ingredient

Benzalkonium Chloride 0.13% w/w. Purpose: Antiseptic

Purpose

Antiseptic

When using this product keep out of eyes, ears, and mouth. In case of contact with eyes, rinse eyes thoroughly with water.

Do not use

- in children less than 2 months of age
- on open skin

Stop use and ask a doctor if irritation or rash occurs. These may be signs of a serious condition.

Keep out of reach of children. If swallowed, get medical help or contact a Poison Control Center right away.

Directions

Unfold towelette, wipe hands, discard after use.

Rub thoroughly into hands for at least 30 seconds, allow to dry.

Directions

Peel back flap on front to pull out a wipe.

Unfold and wipe hands thoroughly.

Reseal and let hands dry.

No need to rinse.

Warnings

For external use only. Flammable. Keep away from heat or flame

- Do not replace wipes used for medical procedures.
- These wipes are meant for general cleansing.

Other information

Store between 15-30℃ (59-86℉)

Inactive ingredients

purified water USP